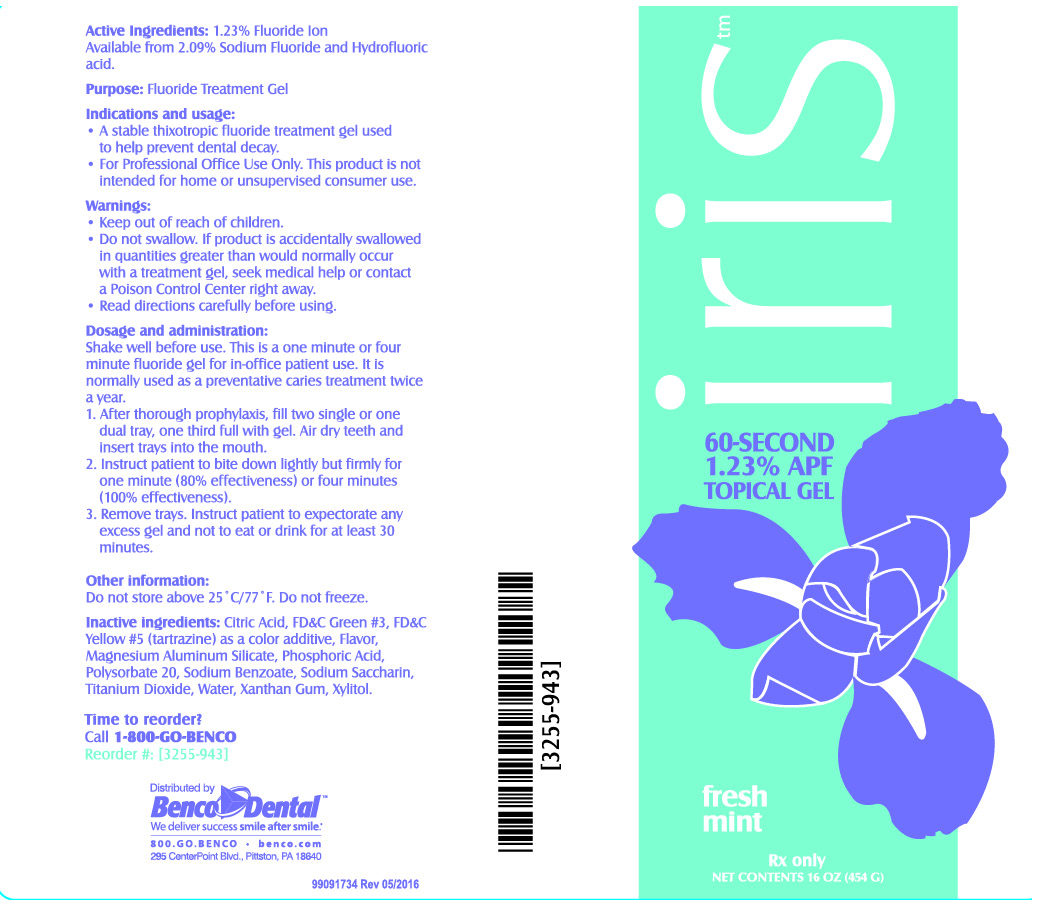 DRUG LABEL: Iris 60 Second APF
NDC: 66975-052 | Form: GEL
Manufacturer: Benco Dental
Category: prescription | Type: HUMAN PRESCRIPTION DRUG LABEL
Date: 20220202

ACTIVE INGREDIENTS: SODIUM FLUORIDE 5.6 g/454 g
INACTIVE INGREDIENTS: CITRIC ACID MONOHYDRATE; MAGNESIUM ALUMINUM SILICATE; PHOSPHORIC ACID; POLYSORBATE 20; SODIUM BENZOATE; SACCHARIN SODIUM; TITANIUM DIOXIDE; WATER; XANTHAN GUM; XYLITOL; FD&C GREEN NO. 3; FD&C YELLOW NO. 5

Active Ingredients:

1.23% Fluoride Ion
Available from 2.09% Sodium Fluoride and Hydrofluoric Acid.

Purpose:

Fluoride Treatment Gel

Indications and usage:

• A stable thixotropic fluoride treatment gel used to help prevent dental decay.
• For Professional Office Use Only. This product is not intended for home or unsupervised consumer use.

Warnings:

• Keep out of reach of children.
• Do not swallow. If product is accidentally swallowed in quantities greater than would normally occur with a treatment gel, seek medical help or contact a Poison Control Center right away.
• Read directions carefully before using.

Dosage and administration:

- Shake well before use. This is a one minute of four minute fluoride gel for in-office patient use. It is normally used as a preventative caries treatment twice a year.
  • After thorough prophylaxis, fill two single or one dual tray, one third full with gel. Air dry teeth and insert trays into the mouth.
  • Instruct patient to bite down lightly but firmly for one minute (80% effectiveness) or four minutes (100% effectiveness).
  • Remove trays. Instruct patient to expectorate any excess gel and not to eat or drink for at least 30 minutes.

Other information:

Do not store above 25°C/77°F. Do not freeze.

Inactive Ingredients:

Citric Acid, FD&C Green #3, FD&C Yellow #5 (tartrazine) as a color additive, Flavor, Magnesium Aluminum Silicate, Phosphoric Acid, Polysorbate 20, Sodium Benzoate, Sodium Saccharin, Titanium Dioxide, Water, Xanthan Gum, Xylitol.